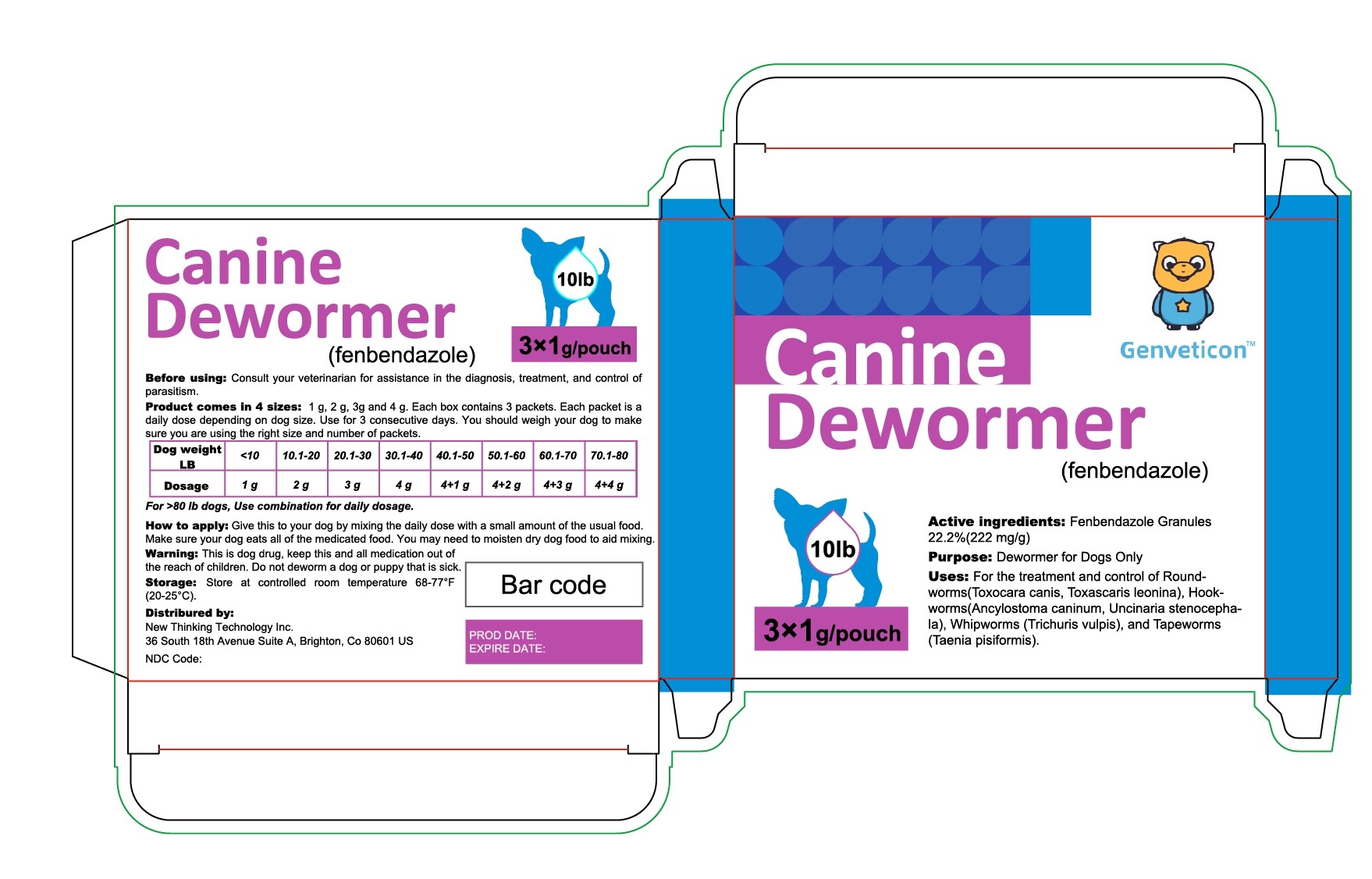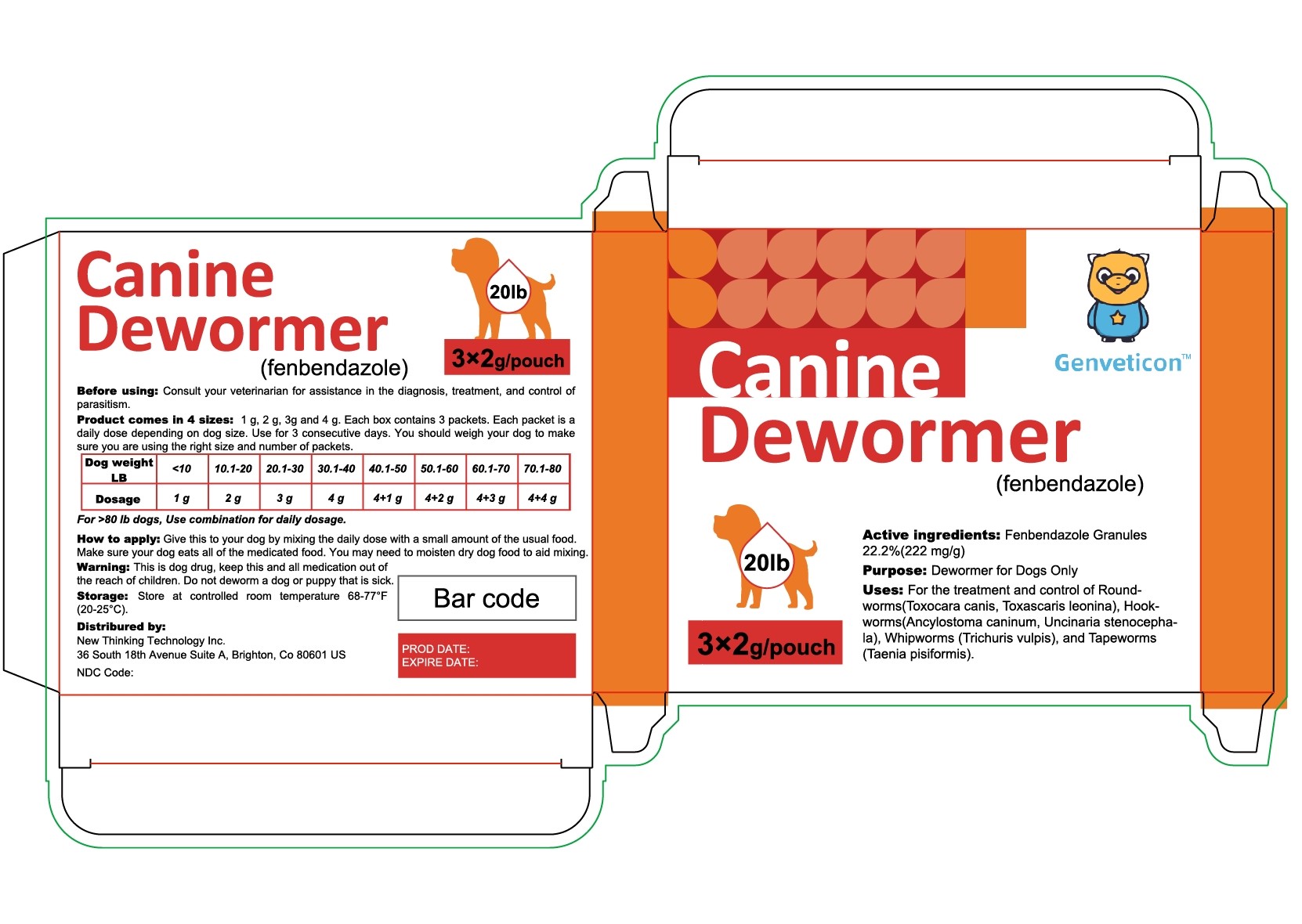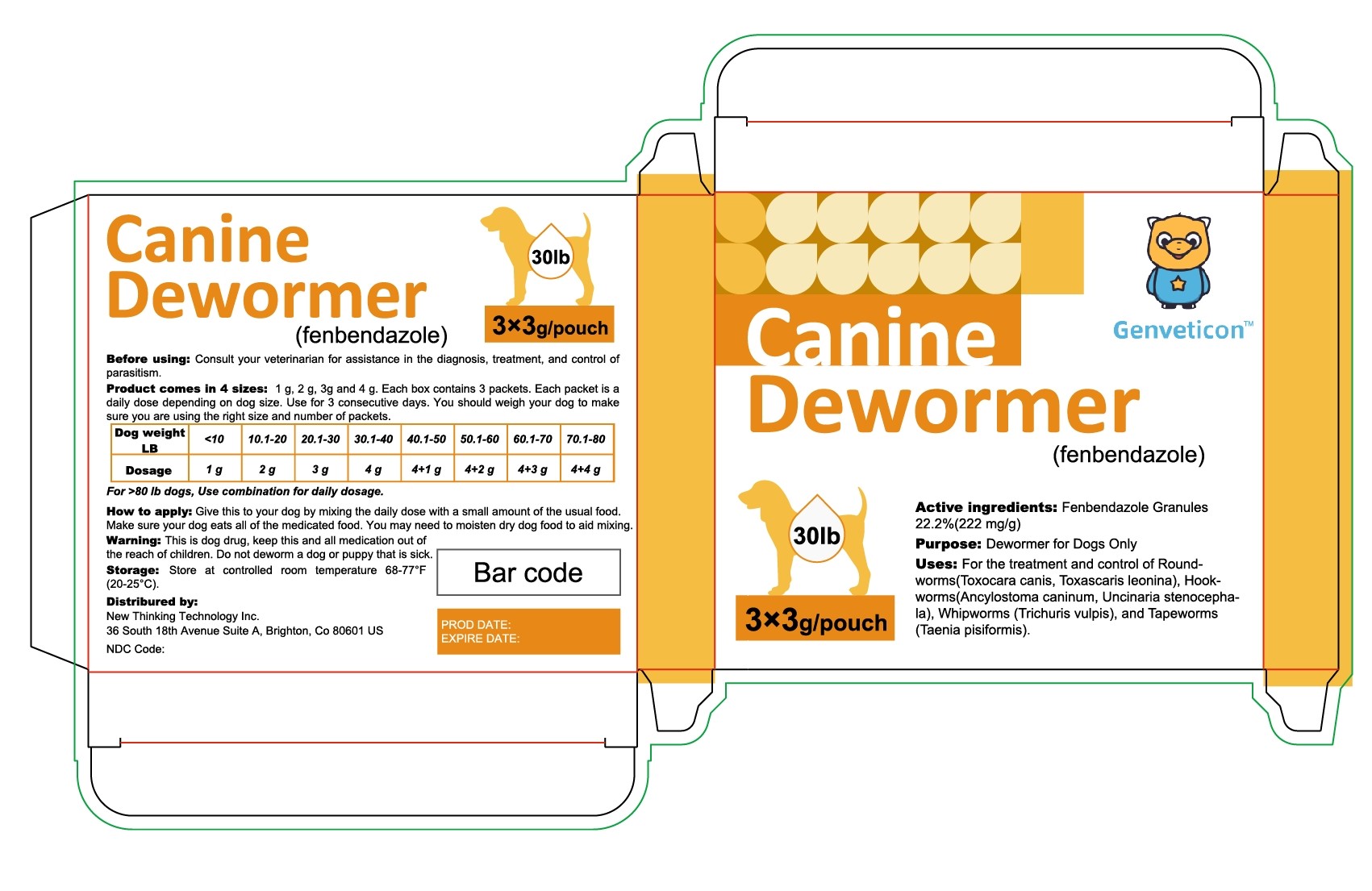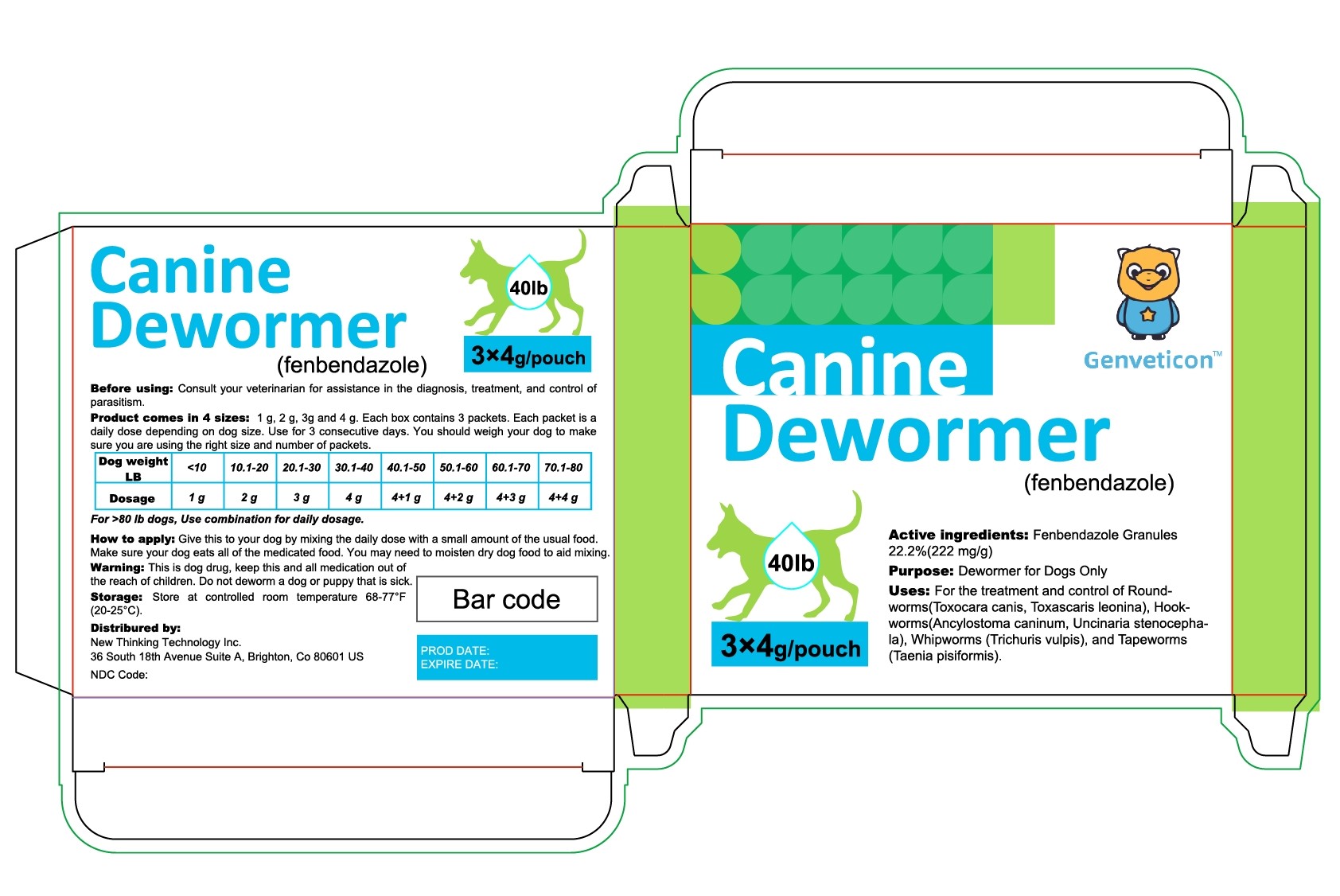 DRUG LABEL: Genveticon Canine Dewormer
NDC: 86216-005 | Form: GRANULE
Manufacturer: Pet Professional inc.
Category: animal | Type: OTC ANIMAL DRUG LABEL
Date: 20250703

ACTIVE INGREDIENTS: FENBENDAZOLE 222 mg/1 g

Genveticon Canine Dewormer

Usage

How to apply: Give this to your dog by mixing the daily dose with a small amount of the usual food. Make sure your dog eats all of the medicated food. You may need to moisten dry dog food to aid mixing.